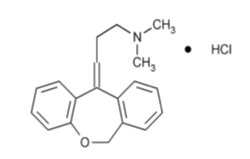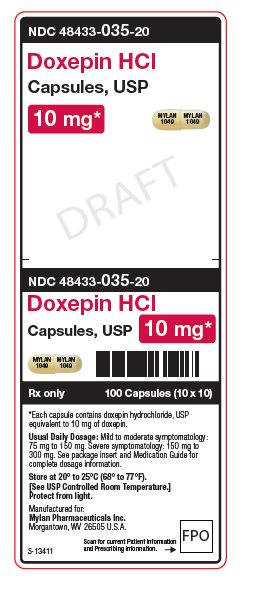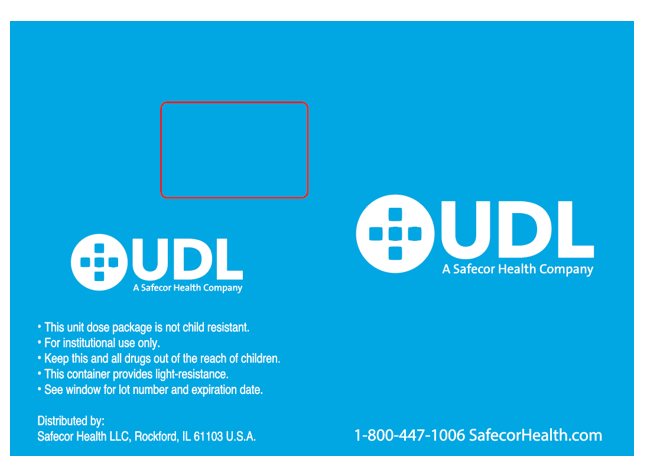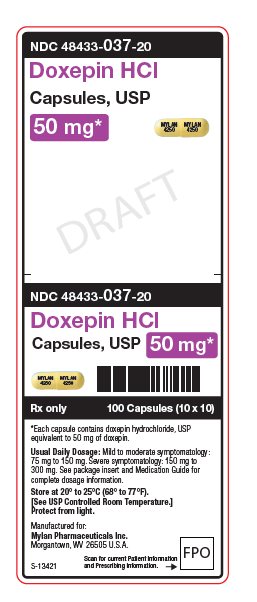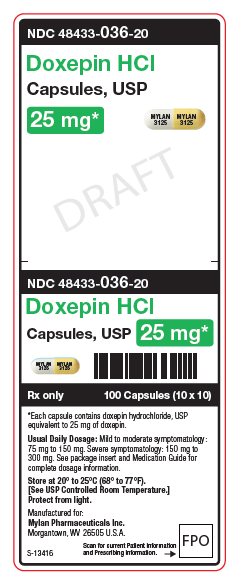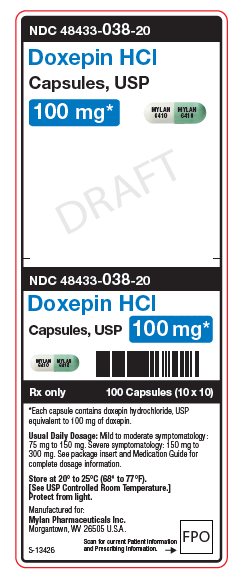 DRUG LABEL: Doxepin Hydrochloride
NDC: 48433-035 | Form: CAPSULE
Manufacturer: Safecor Health, LLC
Category: prescription | Type: HUMAN PRESCRIPTION DRUG LABEL
Date: 20260224

ACTIVE INGREDIENTS: DOXEPIN HYDROCHLORIDE 10 mg/1 1
INACTIVE INGREDIENTS: SILICON DIOXIDE; MAGNESIUM STEARATE; MICROCRYSTALLINE CELLULOSE; STARCH, CORN; SODIUM LAURYL SULFATE; D&C YELLOW NO. 10; GELATIN, UNSPECIFIED; TITANIUM DIOXIDE; FD&C YELLOW NO. 6; FERROSOFERRIC OXIDE; D&C YELLOW NO. 10 ALUMINUM LAKE; FD&C BLUE NO. 1 ALUMINUM LAKE; FD&C BLUE NO. 2 ALUMINUM LAKE; FD&C RED NO. 40; PROPYLENE GLYCOL; SHELLAC

HIGHLIGHTS OF PRESCRIBING INFORMATION

These highlights do not include all the information needed to use DOXEPIN HYDROCHLORIDE CAPSULES safely and effectively. See full prescribing information for DOXEPIN HYDROCHLORIDE CAPSULES.
DOXEPIN HYDROCHLORIDE capsules, for oral use
Initial U.S. Approval: 1969

RECENT MAJOR CHANGES

Dosage and Administration (2.4, 2.5, 2.6, 2.7) 7/2025
Warnings and Precautions (5.2, 5.5) 7/2025

WARNING: SUICIDAL THOUGHTS AND BEHAVIORS

See full prescribing information for complete boxed warning.

- Increased risk of suicidal thoughts and behaviors in pediatric and young adults taking antidepressants. Closely monitor all antidepressant-treated patients for clinical worsening and emergence of suicidal thoughts and behaviors (5.1)
- Doxepin hydrochloride capsules are not approved for use in pediatric patients (8.4)

1 INDICATIONS AND USAGE

Doxepin hydrochloride capsules are a tricyclic antidepressant (TCA) indicated for the treatment of major depressive disorder (MDD) in adults (1).

2 DOSAGE AND ADMINISTRATION

- Prior to initiating treatment with doxepin hydrochloride capsules, screen patients for a personal or family history of bipolar disorder, mania, or hypomania. (2.1)
- Recommended starting oral dosage is 25 mg three times daily or 75 mg once daily. (2.2)
- Recommended target total dosage range is between 75 mg/day and 150 mg/day (may be given once daily or in divided doses). (2.2)
- Maximum recommended dosage is 100 mg three times daily. (2.2)
- Wait at least 14 days after discontinuation of a monoamine oxidase inhibitor (MAOI) before initiating therapy with doxepin hydrochloride capsules. (2.3)
- See the Full Prescribing Information for dosage modifications intended to reduce the risk of anticholinergic effects, for strong CYP2D6 inhibitors, and in known CYP2D6 and CYP2C19 poor metabolizers. (2.4, 2.5, 2.6).
- When discontinuing doxepin hydrochloride capsules, gradually reduce the dosage until discontinued. (2.7)

3 DOSAGE FORMS AND STRENGTHS

- Capsules: 10 mg, 25 mg, 50 mg, 75 mg and 100 mg (3)

4 CONTRAINDICATIONS

- Hypersensitivity to doxepin (4)
- Glaucoma (4)
- Current or past urinary retention (4)
- Taking MAOIs, or within 14 days of stopping MAOIs (4)

5 WARNINGS AND PRECAUTIONS

- Suicidal Thoughts and Behaviors: Monitor for clinical worsening and suicide thoughts and behaviors. Consider changing the therapeutic regimen, including possibly discontinuing doxepin hydrochloride capsules, in patients who are experiencing emergent suicidal thoughts or behaviors. (5.1)
- Serotonin Syndrome: Risk increases with concomitant use of other serotonergic drugs. Monitor all patients taking doxepin hydrochloride capsules for the emergence of serotonin syndrome. Discontinue doxepin hydrochloride capsules and any concomitant serotonergic agents immediately and initiate supportive treatment if serotonin syndrome occurs. (5.2, 7)
- Angle-Closure Glaucoma: Avoid use of doxepin hydrochloride capsules in patients with untreated anatomically narrow angles. (5.3)
- Sedation and Driving Risks: Because doxepin hydrochloride capsules can cause sedation, warn patients against driving a car or operating dangerous machinery while taking doxepin hydrochloride capsules. (5.4)
- Activation of Mania or Hypomania: Prior to initiating antidepressant therapy, screen for bipolar disorder. Doxepin hydrochloride capsules are not approved for use in treating bipolar depression. (5.5)

6 ADVERSE REACTIONS

Most common adverse reactions (incidence ≥ 5%) are somnolence, dry mouth, dizziness, constipation and fatigue. (6.1).

To report SUSPECTED ADVERSE REACTIONS, contact Mylan at 1-877-446-3679 (1-877-4-INFO-RX) or FDA at 1-800-FDA-1088 or www.fda.gov/medwatch.

7 DRUG INTERACTIONS

- Serotonergic Drugs: Monitor patients for signs and symptoms of serotonin syndrome, particularly during treatment initiation and dosage increases. If serotonin syndrome occurs, consider discontinuation of doxepin hydrochloride capsules and/or concomitant serotonergic drugs. (5.2, 7)
- Strong CYP2D6 Inhibitors: Concomitant use of TCAs with drugs that can inhibit CYP2D6 may require lower dosages for the TCA or the other drug, and monitor TCA plasma levels. (7)
- Carbamazepine: Monitor doxepin plasma concentrations and increase doxepin hydrochloride capsules dosage in patients taking carbamazepine. (7)
- Cimetidine: Monitor doxepin plasma concentrations and consider reducing the doxepin hydrochloride capsules dosage in patients taking cimetidine. (7)
- Alcohol: Avoid concomitant use. (7)
- CNS Depressants: Dosage reduction may be needed based on clinical response and tolerability. (7)
- Tolazamide: Monitor glucose levels and reduce the doxepin hydrochloride capsules dosage as appropriate. (7)

8 USE IN SPECIFIC POPULATIONS

- Pregnancy: Neonates exposed to TCAs, including doxepin hydrochloride capsules, late in the third trimester have developed poor adaptation (respiratory distress, temperature instability, feeding difficulty, hypotonia, irritability). Monitor neonates who were exposed to doxepin hydrochloride capsules in the third trimester of pregnancy for poor neonatal adaptation syndrome. (8.1)
- Lactation: Breastfeeding not recommended. (8.2)
- Geriatric Use: May cause confusion and oversedation. (8.5)
- CYP2C19 and CYP2D6 Poor Metabolizers: Increased risk of doxepin hydrochloride capsule-associated adverse reactions. (8.7)

FULL PRESCRIBING INFORMATION

WARNING: SUICIDAL THOUGHTS AND BEHAVIORS

Antidepressants increase the risk of suicidal thoughts and behavior in pediatric and young adult patients in short-term studies. Closely monitor all antidepressant-treated patients for clinical worsening and emergence of suicidal thoughts and behaviors [see Warnings and Precautions (5.1)]. Doxepin hydrochloride capsules are not approved for use in pediatric patients [see Use in Specific Populations (8.4)].

1 INDICATIONS AND USAGE

Doxepin hydrochloride capsules are indicated for the treatment of major depressive disorder (MDD) in adults.

2 DOSAGE AND ADMINISTRATION

2.1 Screen for Bipolar Disorder Prior to Starting Doxepin Hydrochloride Capsules

Prior to initiating treatment with doxepin hydrochloride capsules, screen patients for a personal or family history of bipolar disorder, mania, or hypomania [see Warnings and Precautions (5.5)].

2.2 Recommended Dosage

The recommended starting oral dosage for doxepin hydrochloride capsules is 25 mg three times daily or 75 mg once daily. The recommended target total oral dosage range for doxepin hydrochloride capsules is between 75 mg/day and 150 mg/day (may be given once daily or in divided doses). The maximum recommended oral dosage for doxepin hydrochloride capsules is 100 mg three times daily.

2.3 Switching Patients to or from a Monoamine Oxidase Inhibitor

Wait at least 14 days after discontinuation of a monoamine oxidase inhibitor (MAOI) before initiating therapy with doxepin hydrochloride capsules [see Contraindications (4), Warnings and Precautions (5.2), and Drug Interactions (7)] .

Wait at least 14 days after discontinuation of doxepin hydrochloride capsules before initiating therapy with an MAOI [see Contraindications (4), Warnings and Precautions (5.2), and Drug Interactions (7)].

2.4 Dosage Modifications Intended to Reduce the Risk of Anticholinergic Effects

If anticholinergic effects (e.g., dry mouth, blurred vision, constipation) develop, reduce the doxepin hydrochloride capsules dosage [see Adverse Reactions (6.1)].

2.5 Dosage Modifications for Strong CYP2D6 Inhibitors

Reduce the doxepin hydrochloride capsules dosage based on doxepin plasma concentrations when used concomitantly with strong CYP2D6 inhibitors [see Drug Interactions (7)].

2.6 Dosage Modifications in Known CYP2D6 and CYP2C19 Poor Metabolizers

Reduce the doxepin hydrochloride capsules dosage based on doxepin plasma concentrations in patients who are known CYP2D6 and CYP2C19 poor metabolizers [see Use in Specific Populations (8.7)].

2.7 Discontinuation of Doxepin Hydrochloride Capsules Treatment

When discontinuing doxepin hydrochloride capsules, gradually reduce the dosage until discontinued [see Adverse Reactions (6)] .

3 DOSAGE FORMS AND STRENGTHS

Doxepin Hydrochloride Capsules, USP are available containing doxepin hydrochloride, USP equivalent to 10 mg, 25 mg, 50 mg, 75 mg or 100 mg of doxepin.

- The 10 mg capsules are hard-shell, gelatin capsules with a buff opaque cap and buff opaque body axially printed with MYLANover 1049in black ink on both the cap and the body.
- The 25 mg capsules are hard-shell, gelatin capsules with an ivory opaque cap and white opaque body axially printed with MYLANover 3125in black ink on both the cap and the body.
- The 50 mg capsules are hard-shell, gelatin capsules with an ivory opaque cap and ivory opaque body axially printed with MYLANover 4250in black ink on both the cap and the body.
- The 75 mg capsules are hard-shell, gelatin capsules with a brite lite green opaque cap and brite lite green opaque body axially printed with MYLANover 5375in black ink on both the cap and the body.
- The 100 mg capsules are hard-shell, gelatin capsules with a brite lite green opaque cap and white opaque body axially printed with MYLANover 6410in black ink on both the cap and the body.

4 CONTRAINDICATIONS

Doxepin hydrochloride capsules are contraindicated in patients:

- With hypersensitivity to doxepin (hypersensitivity reactions have included tongue edema and urticaria). The possibility of cross sensitivity with other dibenzoxepines should be kept in mind.
- With glaucoma [see Warnings and Precautions (5.3)].
- With current or past urinary retention [see Adverse Reactions (6.1)].
- Taking MAOIs, or within 14 days of stopping MAOIs (including the MAOIs linezolid or intravenous methylene blue) because of an increased risk of serotonin syndrome [see Warnings and Precautions (5.2)and Drug Interactions (7)].

5 WARNINGS AND PRECAUTIONS

5.1 Suicidal Thoughts and Behaviors in Adolescents and Young Adults

In pooled analyses of placebo-controlled trials of antidepressant drugs including tricyclic antidepressants and other antidepressant classes that included approximately 77,000 adult patients and 4,500 pediatric patients (doxepin hydrochloride capsules are not approved for use in pediatric patients), the incidence of suicidal thoughts and behaviors in antidepressant-treated patients age 24 years and younger was greater than in placebo-treated patients. There was considerable variation in risk of suicidal thoughts and behaviors among drugs, but there was an increased risk identified in young patients for most drugs studied. The drug-placebo differences in the number of cases of suicidal thoughts and behaviors per 1,000 patients treated are provided in Table 1.

Table 1: Risk Differences of the Number of Patients of Suicidal Thoughts and Behaviors in the Pooled Placebo-Controlled Trials of Antidepressants in Pediatric and Adult Patients
Age Range | Drug-Placebo Difference in Number of Patients of Suicidal Thoughts or Behaviors per 1,000 Patients Treated
 | Increases Compared to Placebo
< 18 years old | 14 additional patients
18-24 years old | 5 additional patients
 | Decreases Compared to Placebo
25-64 years old | 1 fewer patient
≥ 65 years old | 6 fewer patients

It is unknown whether the risk of suicidal thoughts and behaviors in pediatric and young adults extends to longer-term use, i.e., beyond four months. However, there is substantial evidence from placebo-controlled maintenance trials in adults with MDD that antidepressants delay the recurrence of depression.

Monitor all doxepin hydrochloride capsules-treated patients for clinical worsening and emergence of suicidal thoughts and behaviors, especially during the initial few months of doxepin hydrochloride capsules therapy, and at times of dosage changes. Counsel family members or caregivers of patients to monitor for changes in behavior and to alert the health care provider. Consider changing the therapeutic regimen, including possibly discontinuing doxepin hydrochloride capsules, in patients who are experiencing emergent suicidal thoughts or behaviors.

5.2 Serotonin Syndrome

Tricyclic antidepressants, including doxepin hydrochloride capsules, can precipitate serotonin syndrome, a potentially life-threatening condition. This risk is increased with concomitant use of other serotonergic drugs (e.g., other tricyclic antidepressants, SSRIs, serotonin norepinephrine reuptake inhibitors, triptans, tetracyclic antidepressants, opioids), lithium, tryptophan, buspirone, and St. John’s Wort) and with drugs that impair metabolism of serotonin (e.g., MAOIs intended to treat psychiatric disorders and others, such as linezolid or intravenous methylene blue) [see Drug Interactions (7)] .

Serotonin syndrome symptoms may include mental status changes (e.g., confusion, agitation, hallucinations, delirium, and coma), autonomic instability (e.g., tachycardia, labile blood pressure, hyperthermia, diaphoresis, and flushing), neuromuscular abnormalities (e.g., tremor, rigidity, clonus, and hyperreflexia), seizures and gastrointestinal signs and symptoms (e.g., nausea, vomiting, diarrhea). Patients should be monitored for the emergence of serotonin syndrome.

The concomitant use of doxepin hydrochloride capsules with MAOIs is contraindicated. The use of doxepin hydrochloride capsules within 14 days of discontinuing treatment with an MAOI intended to treat psychiatric disorders is contraindicated. Starting doxepin hydrochloride capsules in a patient who is being treated with an MAOI such as linezolid or intravenous methylene blue is contraindicated. No reports involved the administration of methylene blue by other routes (such as oral or local tissue injection). If it is necessary to initiate treatment with a MAOI such as linezolid or intravenous methylene blue in a patient taking doxepin hydrochloride capsules, discontinue doxepin hydrochloride capsules before initiating treatment with the MAOI [see Dosage and Administration (2.4)and Drug Interactions (7)] .

Monitor all patients taking doxepin hydrochloride capsules for the emergence of serotonin syndrome. Discontinue doxepin hydrochloride capsules treatment and any concomitant serotonergic agents immediately if the above symptoms occur, and initiate supportive symptomatic treatment. If concomitant use of doxepin hydrochloride capsules with other serotonergic drugs (besides MAOIs which are contraindicated) is clinically warranted, inform patients of the increased risk for serotonin syndrome and monitor for symptoms.

5.3 Angle-Closure Glaucoma

The pupillary dilation that occurs following use of many antidepressant drugs including doxepin hydrochloride capsules may trigger an angle closure glaucoma attack in a patient with anatomically narrow angles who does not have a patent iridectomy. Patients may wish to be examined to determine whether they are susceptible to angle closure, and have a prophylactic procedure (e.g., iridectomy), if they are susceptible.

Doxepin hydrochloride capsules are contraindicated in patients with glaucoma. Avoid use of doxepin hydrochloride capsules in patients with untreated anatomically narrow angles.

5.4 Sedation and Driving Risks

Because doxepin hydrochloride capsules can cause sedation, warn patients of the risk of sedation and caution patients against driving a car or operating dangerous machinery while taking doxepin hydrochloride capsules. Also caution patients that their response to alcohol may be potentiated.

Sedating drugs, including doxepin hydrochloride capsules, may cause oversedation in geriatric patients.

5.5 Activation of Mania or Hypomania

In patients with bipolar disorder, treating MDD with doxepin hydrochloride capsules may precipitate a mixed/manic episode. Prior to initiating treatment with doxepin hydrochloride capsules, screen patients for any personal or family history of bipolar disorder, mania, or hypomania. doxepin hydrochloride capsules are not approved for use in treating bipolar depression.

5.6 Risk of Seizures

Caution should be used when doxepin hydrochloride capsules are given to patients with a history of seizure disorder, because this drug may lower the seizure threshold. Patients with a history of seizures should be monitored during doxepin hydrochloride capsules use to identify recurrence of seizures or increase in frequency of seizures.

5.7 Psychosis

In patients with schizophrenia, treatment with doxepin hydrochloride capsules for MDD may activate psychosis. If this occurs, stop doxepin hydrochloride capsules and consider alternative treatment options.

6 ADVERSE REACTIONS

The following clinically significant adverse reactions are described elsewhere in the labeling:

- Suicidal Thoughts and Behaviors in Adolescents and Young Adults [see Warnings and Precautions (5.1)]
- Serotonin Syndrome [see Warnings and Precautions (5.2)]
- Angle-Closure Glaucoma [see Warnings and Precautions (5.3)]
- Sedation and Driving Risks [see Warnings and Precautions (5.4)]
- Activation of Mania or Hypomania [see Warnings and Precautions (5.5)]
- Risk of Seizures [see Warnings and Precautions (5.6)]
- Psychosis [see Warnings and Precautions (5.7)]

6.1 Clinical Trials Experience

Because clinical trials are conducted under widely varying conditions, adverse reaction rates observed in the clinical trials of a drug cannot be directly compared to rates in the clinical trials of another drug and may not reflect the rates observed in practice.

Adverse reactions (≥ 2% of doxepin-treated patients) in 1,635 doxepin-treated patients with MDD in clinical trials included somnolence (17%), dry mouth (15%), dizziness (6%), constipation (5%), fatigue (5%), blurred vision (3%), tachycardia (3%), hypotension (3%), insomnia (2%), tremor (2%), nausea (2%), hyperhidrosis (2%), and increased weight (2%).

Other Adverse Reactions Observed in Clinical Trials

Other adverse reactions that occurred at an incidence of < 2% in patients treated with doxepin in clinical trials were:

- Ear and Labyrinth Disorders: Tinnitus.
- Gastrointestinal Disorders: Diarrhea, dyspepsia, vomiting.
- General Disorders and Administration Site Conditions: Asthenia, edema, chills.
- Metabolism and Nutrition Disorders: Decreased appetite.
- Nervous System Disorders: Ataxia, paresthesia, headache, extrapyramidal disorder.
- Psychiatric Disorders: Agitation, confusional state, libido decreased.
- Pulmonary Disorders: Asthma exacerbation.
- Renal and Urinary Disorders: Urinary retention.
- Reproductive System and Breast Disorders: Breast enlargement.
- Skin & Subcutaneous Tissue Disorders: Rash, pruritus.
- Vascular Disorders: Flushing.

6.2 Postmarketing Experience

The following adverse reactions have been identified during post-approval use of doxepin. Because these reactions are reported voluntarily from a population of uncertain size, it is not always possible to reliably estimate their frequency or establish a causal relationship to drug exposure.

- Blood and Lymphatic System Disorders: Agranulocytosis, leukopenia, thrombocytopenia, eosinophilia, purpura.
- Cardiac Disorders: Conduction disorder, arrhythmia.
- Endocrine Disorders: Inappropriate antidiuretic hormone secretion.
- Eye Disorders: Angle-closure glaucoma, mydriasis.
- Gastrointestinal Disorders: Aphthous stomatitis, abdominal pain upper.
- General Disorders and Administration Site Conditions: Facial edema, hyperpyrexia.
- Hepatobiliary Disorders: Jaundice.
- Investigations: Blood glucose increased.
- Nervous System Disorders: Hypoesthesia, dysgeusia, convulsion, tardive dyskinesia, serotonin syndrome.
- Psychiatric Disorders: Hallucination, disorientation.
- Reproductive System and Breast Disorders: Testicular swelling, gynecomastia, galactorrhea.
- Skin and Subcutaneous Tissue Disorders: Photosensitivity reaction, tongue edema, alopecia, urticaria.
- Vascular Disorders: Hypertension.

Withdrawal syndrome occurred after stopping doxepin [see Drug Abuse and Dependence (9.3)].

The following adverse reaction has been reported with use with other tricyclic antidepressants: decreased blood glucose.

7 DRUG INTERACTIONS

Table 2 describe the clinically significant drug interactions of doxepin hydrochloride capsules with other drugs or classes.

Table 2: Clinically Significant Drug Interactions with Doxepin Hydrochloride Capsules
Monoamine Oxidase Inhibitors
Prevention or Management | Doxepin hydrochloride capsules are contraindicated in patients taking monoamine oxidase inhibitors (MAOIs), including MAOIs such as linezolid or intravenous methylene blue. The use of doxepin hydrochloride capsules within 14 days of discontinuation of an MAOI or the use of MAOI within 14 days of discontinuation of doxepin hydrochloride capsules is contraindicated .Starting doxepin hydrochloride capsules in a patient who is being treated with an MAOI is contraindicated .
Clinical Effect(s) | Concomitant use of doxepin hydrochloride capsules and MAOIs increases the risk of serotonin syndrome [ Warnings and Precautions (5.2)] .
Other Serotonergic Drugs (Besides MAOIs)
Prevention or Management | Monitor patients for signs and symptoms of serotonin syndrome, particularly during treatment initiation and dosage increases. If serotonin syndrome occurs, consider discontinuation of doxepin hydrochloride capsules and/or concomitant serotonergic drugs [see Warnings and Precautions (5.2)].
Mechanism and Clinical Effect(s) | Concomitant use of doxepin hydrochloride capsules with other serotonergic drugs increases the risk of serotonin syndrome [see Warnings and Precautions (5.2)].
Strong CYP2D6 Inhibitors
Prevention or Management | Monitor doxepin plasma concentrations and reduce the doxepin hydrochloride capsules dosage or the strong CYP2D6 inhibitor as appropriate [see Dosage and Administration (2.5)].
Mechanism and Clinical Effect(s) | Concomitant use of doxepin hydrochloride capsules with strong CYP2D6 inhibitors may increase the exposures of doxepin [see Clinical Pharmacology (12.3)] which may increase the risk of doxepin hydrochloride capsules related adverse reactions [see Warnings and Precautions (5)and Adverse Reactions (6)].
Examples | See www.fda.gov/CYPandTransporterInteractingDrugs for examples of strong CYP2D6 Inhibitors.
Carbamazepine
Prevention or Management | Monitor doxepin plasma concentrations and consider increasing the doxepin hydrochloride capsules dosage in patients taking carbamazepine.
Mechanism and Clinical Effect(s) | Concomitant use of carbamazepine with doxepin hydrochloride capsules decreases the exposure of doxepin [see Clinical Pharmacology (12.3)] which could lead to reduced treatment effect.
Cimetidine
Prevention or Management | Monitor doxepin plasma concentrations and consider reducing the doxepin hydrochloride capsules dosage in patients taking cimetidine.
Mechanism and Clinical Effect(s) | Concomitant use of doxepin hydrochloride capsules with cimetidine may increase the exposures of doxepin [see Clinical Pharmacology (12.3)] which may increase the risk of doxepin hydrochloride capsules-related anticholinergic effects (e.g., dry mouth, blurred vision, constipation) [see Adverse Reactions (6.1)].
Alcohol
Prevention or Management | Avoid concomitant use with alcohol.
Mechanism and Clinical Effect(s) | Doxepin hydrochloride capsules may potentiate the sedative effects of alcohol [see Warnings and Precautions (5.4)] .
CNS Depressants
Prevention or Management | Dosage reduction of doxepin hydrochloride capsules and/or the CNS depressant may be needed based on clinical response and tolerability.
Mechanism and Clinical Effect(s) | When concomitantly administered with doxepin hydrochloride capsules, the sedative effects of CNS depressant may be potentiated [see Warnings and Precautions (5.4)] .
Tolazamide
Prevention or Management | Monitor glucose levels and reduce the doxepin hydrochloride capsules dosage as appropriate.
Clinical Effect(s) | Doxepin hydrochloride capsules may cause severe hypoglycemia when concomitantly used with tolazamide.

8 USE IN SPECIFIC POPULATIONS

8.1 Pregnancy

Pregnancy Exposure Registry

There is a pregnancy exposure registry that monitors pregnancy outcomes in women exposed to antidepressants, including doxepin hydrochloride capsules, during pregnancy. Health care providers are encouraged to advise patients to register by calling the National Pregnancy Registry for Antidepressants 1-866-961-2388 or visiting online at https://womensmentalhealth.org/clinical-and-researchprograms/pregnancyregistry/antidepressants.

Risk Summary

Available data from published epidemiological studies and postmarketing reports have not established an increased risk for major birth defects or miscarriage with doxepin hydrochloride capsules use (see Data). There are risks (see Clinical Considerations) :

- To the mother associated with untreated depression in pregnancy.
- Poor neonate adaptation from exposure to tricyclic antidepressants (TCAs), including doxepin hydrochloride capsules, during the third trimester of pregnancy .

Animal reproduction toxicity of doxepin has not been fully characterized.

The background risk of major birth defects and miscarriage for the indicated population is unknown. All pregnancies have a background risk of major birth defect, loss, or other adverse outcomes. In the U.S. general population, the estimated background risk of major birth defects and miscarriage in clinically recognized pregnancies is 2 to 4% and 15 to 20%, respectively.

Clinical Considerations

Disease-associated Maternal and/or Embryofetal Risk

Women who discontinue antidepressants during pregnancy are more likely to experience a relapse of MDD than women who continue antidepressants. This finding is from a prospective longitudinal study of 201 pregnant women with a history of MDD who were euthymic and taking antidepressants at the beginning of pregnancy. Consider the risk of untreated MDD when considering discontinuation of doxepin drugs during pregnancy and the postpartum period.

Fetal/Neonatal Adverse Reactions

Neonates previously exposed to TCAs, including doxepin hydrochloride capsules, late in the third trimester during pregnancy have developed complications requiring prolonged hospitalization, respiratory support, and tube feeding. Such complications can arise immediately upon delivery. Reported clinical findings have included respiratory distress, cyanosis, apnea, seizures, temperature instability, feeding difficulty, vomiting, hypoglycemia, hypotonia, hypertonia, hyperreflexia, tremor, jitteriness, irritability, and constant crying. These findings are consistent with either direct toxic effects of TCAs or possibly a drug discontinuation syndrome. Monitor neonates who were exposed to doxepin hydrochloride capsules in the third trimester of pregnancy for poor neonatal adaptation syndrome.

Data

Human Data

Published epidemiological studies of pregnant women exposed to TCAs, including doxepin hydrochloride capsules, have not established an association with major birth defects, miscarriage, or adverse maternal outcomes. Methodological limitations of these observational studies include small sample size and lack of adequate controls.

8.2 Lactation

Risk Summary

Data from published literature report the presence of doxepin and nordoxepin in human milk. There are reports of excessive sedation, respiratory depression, poor suckling and swallowing and hypotonia in breastfed infants exposed to doxepin at doses used to treat MDD. There are no data on the effects of doxepin on milk production.

Because of the potential for serious adverse reactions, including excess sedation and respiratory depression in a breastfed infant, advise patients that breastfeeding is not recommended during doxepin hydrochloride capsules treatment.

8.4 Pediatric Use

The safety and effectiveness of doxepin hydrochloride capsules in pediatric patients have not been established.

Antidepressants increase the risk of suicidal thoughts and behaviors in pediatric patients [see Warnings and Precautions (5.1)] .

8.5 Geriatric Use

Clinical studies of doxepin did not include sufficient numbers of patients 65 years of age and older to determine whether they respond differently from younger adult patients.

Sedating drugs, including doxepin hydrochloride capsules, may cause confusion and oversedation in geriatric patients. The recommended starting doxepin hydrochloride capsules dosage in geriatric patients is generally lower than those of younger adult patients .

8.6 Hepatic Impairment

The effect of hepatic impairment (HI) on the pharmacokinetics of doxepin has not been studied. Doxepin is primarily metabolized in the liver. Doxepin hydrochloride capsules-treated patients with HI may have a greater systemic doxepin exposure than those with normal liver function. Consider obtaining doxepin concentrations in patients with HI and modifying the dosage as appropriate.

8.7 Use in Genomic Subgroups

The recommended doxepin hydrochloride capsules dosage in CYP2C19 and CYP2D6 poor metabolizers is lower than the recommended dosage in CYP2C19 and CYP2D6 normal metabolizers [see Dosage and Administration (2.6)].

According to the literature, doxepin is primarily metabolized by CYP2D6 and/or CYP2C19; thus, the use of doxepin hydrochloride capsules in CYP2D6 and/or CYP2C19 poor metabolizers will likely result in higher doxepin exposures and an increased risk of doxepin hydrochloride capsule-associated adverse reactions.

9 DRUG ABUSE AND DEPENDENCE

9.1 Controlled Substance

Doxepin hydrochloride capsules contain doxepin, which is not a controlled substance.

9.2 Abuse

Doxepin hydrochloride capsules are not associated with abuse.

9.3 Dependence

Physical dependence is a state that develops as a result of physiological adaptation in response to repeated drug use, manifested by withdrawal signs and symptoms after abrupt discontinuation or a significant dose reduction of a drug. Abrupt cessation of doxepin hydrochloride capsules after prolonged administration can result in withdrawal symptoms, which is indicative of physical dependence.

10 OVERDOSAGE

Signs, Symptoms, and Complications of Doxepin Hydrochloride Capsules Overdose

Serious manifestations of tricyclic antidepressant (TCA) overdose include cardiac dysrhythmias, severe hypotension, convulsions, and CNS depression, including coma. Deaths may occur from overdosage with TCAs, including doxepin hydrochloride capsules. Changes in the electrocardiogram, particularly in QRS axis or width, are clinically significant indicators of TCA toxicity. A maximal limb-lead QRS duration of ≥ 0.1 seconds may be the best indication of the TCA overdose severity.

Signs and symptoms of TCA toxicity develop rapidly after TCA overdose. Other signs of TCA overdose may include confusion, disturbed concentration, transient visual hallucinations, dilated pupils, agitation, hyperactive reflexes, stupor, drowsiness, muscle rigidity, vomiting, hypothermia, or hyperpyrexia. There are reports of patients succumbing to fatal dysrhythmia late after TCA overdose.

Management of Overdose

The following are recommendations for the management of a doxepin hydrochloride capsules overdose. Contact the Poison Help line (1-800-222-1222) or a medical toxicologist for additional overdose management recommendations.

With a doxepin hydrochloride capsules overdose, obtain an ECG and immediately initiate cardiac monitoring in the hospital. A minimum of six hours of observation with cardiac monitoring and observation for signs of CNS depression, respiratory depression, hypotension, cardiac dysrhythmias, conduction blocks, and seizures is recommended. If signs of toxicity occur during this period, extended monitoring is recommended.

Monitoring of plasma doxepin levels should not guide doxepin hydrochloride capsules overdose management.

Cardiovascular Toxicity Management:Intravenous sodium bicarbonate should be administered to maintain the serum pH in the range of 7.45 to 7.55. If the pH response is inadequate to intravenous sodium bicarbonate therapy, hyperventilation may also be used. With concomitant use of hyperventilation and sodium bicarbonate therapy frequently monitor pH and pCO2. A pH > 7.6 or a pCO2 < 20 mm Hg is undesirable. Dysrhythmias unresponsive to intravenous sodium bicarbonate therapy/hyperventilation may respond to lidocaine therapy. Type 1A and 1C antiarrhythmics are generally contraindicated (e.g., quinidine, disopyramide, and procainamide) in the setting of TCA overdose. Hemodialysis, peritoneal dialysis, exchange transfusions, and forced diuresis generally have been reported as ineffective in TCA overdose due to high tissue and protein binding of doxepin.

CNS Toxicity Management:In patients with TCA overdose who have CNS depression, early intubation is recommended because of the potential for abrupt deterioration. Seizures should be controlled with benzodiazepines, or if these are ineffective, other anticonvulsants (e.g., phenobarbital, propofol). Avoid use of physostigmine to treat TCA overdose.

11 DESCRIPTION

Doxepin is a tricyclic antidepressant.

The molecular formula of doxepin hydrochloride is C19H21NO • HCl with a molecular weight of 315.84. It is a white crystalline powder freely soluble in water, in ethanol (96%), and methylene chloride. Doxepin is a dibenzoxepin derivative. Specifically, it is an isomeric mixture of: 1-Propanamine, 3-dibenz[ b, e]oxepin-11(6 H)ylidene- N, N-dimethyl-, hydrochloride. The structural formula of doxepin is shown below.

Doxepin hydrochloride capsules are for oral administration.

Active ingredients for the capsules include: 10 mg, 25, mg, 50 mg, 75 mg and 100 mg of doxepin (equivalent to 11.4 mg, 28.5 mg, 57 mg, 85.5 mg and 114 mg of doxepin hydrochloride, respectively).

Capsule inactive ingredients: colloidal silicon dioxide, magnesium stearate, microcrystalline cellulose, pregelatinized starch (corn) and sodium lauryl sulfate. The empty gelatin capsule shells contain D&C Yellow No. 10, gelatin, sodium lauryl sulfate and titanium dioxide. In addition, the 10 mg, 25 mg and 50 mg empty gelatin capsule shells contain FD&C Yellow No. 6 and the 75 mg and 100 mg empty gelatin capsule shells contain FD&C Green No. 3.

The imprinting ink contains black iron oxide, D&C Yellow No. 10 Aluminum Lake, FD&C Blue No. 1 Aluminum Lake, FD&C Blue No. 2 Aluminum Lake, FD&C Red No. 40 Aluminum Lake, propylene glycol and shellac glaze.

12 CLINICAL PHARMACOLOGY

12.1 Mechanism of Action

The mechanism of action of the doxepin hydrochloride capsules in the treatment of MDD in adult patients is not well understood.

12.2 Pharmacodynamics

The exposure-response relationship and time course of pharmacodynamic response for the safety and effectiveness of doxepin have not been fully characterized.

12.3 Pharmacokinetics

Absorption

In healthy volunteers, a single oral doxepin hydrochloride capsule dose of 75 mg resulted in peak plasma doxepin concentrations that ranged from 8.8 ng/mL to 45.8 ng/mL (mean 26.1 ng/mL). Peak levels were reached between 2 and 4 hours (mean 2.9 hours) after doxepin hydrochloride capsules administration. Peak levels for the primary active metabolite N-desmethyldoxepin (nordoxepin) ranged from 4.8 ng/mL to 14.5 ng/mL (mean 9.7 ng/mL) and were achieved between 2 and 10 hours after doxepin hydrochloride capsules administration.

Distribution

The mean apparent volume of distribution for doxepin was approximately 20 L/kg. The protein binding for doxepin was approximately 76%.

Elimination

In healthy volunteers, the plasma elimination half-life of doxepin ranged from 8 to 24 hours (mean 17 hours). The half-life of nordoxepin ranged from 33 to 80 hours (mean 51 hours). The mean plasma clearance for doxepin was approximately 0.84 L/hour/kg.

Metabolism

After oral doxepin administration, approximately 55% to 87% of doxepin undergoes first-pass metabolism in the liver, forming the primary active metabolite nordoxepin. Metabolic pathways of doxepin include demethylation, N-oxidation, hydroxylation and glucuronide formation.

Excretion

Doxepin is excreted primarily in the urine, mainly as its metabolites, either free or in conjugate form.

Specific Populations

Patients with Hepatic Impairment

Specific clinical studies have not been performed to evaluate the pharmacokinetics of doxepin in patients with hepatic impairment. Patients with hepatic impairment may have a greater systemic doxepin exposure than those with normal liver function [see Use in Specific Populations (8.6)].

Patients with Renal Impairment

The extent of renal excretion of doxepin is unknown. Specific clinical studies have not been performed to evaluate the pharmacokinetics of doxepin in patients with renal impairment compared to those with normal renal function.

Drug Interaction Studies

Carbamazepine

After concomitant use of doxepin and carbamazepine, the combined exposure of doxepin and nordoxepin (12 hours after the last dose) was decreased by 55% compared to that after the use of doxepin alone [see Drug Interactions (7)].

Strong CYP2D6 Inhibitors

CYP2D6 contributes to the metabolism of doxepin and concomitant use of doxepin with strong CYP2D6 inhibitors may increase doxepin exposure [see Drug Interactions (7)].

Cimetidine

Cimetidine is a non-specific inhibitor of CYP1A2, 2C19, 2D6, and 3A4. When cimetidine 300 mg twice daily was administered concomitantly with a single 6 mg dose of another oral doxepin product, there was approximately a 2-fold increase in doxepin Cmaxand AUC compared to doxepin without cimetidine [see Drug Interactions (7)] .

CYP2D6 Substrates:

Concomitant use of doxepin and other CYP2D6 substrates may have impact on the plasma doxepin concentrations. The clinical significance of this possible impact is unknown.

13 NONCLINICAL TOXICOLOGY

13.1 Carcinogenesis, Mutagenesis, Impairment of Fertility

Carcinogenesis

The carcinogenic potential of doxepin in animals has not been fully characterized.

Mutagenesis

The mutagenetic potential of doxepin in animals has not been fully characterized.

Impairment of Fertility

Doxepin had no effect on female fertility in rats at oral doses up to 25 mg/kg/day (1.6x the human dose of 150 mg/day on a mg/m^2basis for a 60 kg human).

Insemination and conception were reduced in untreated female rats mated with male rats administered doxepin at 25 mg/kg/day for a period of ≥ 7 months.

16 HOW SUPPLIED/STORAGE AND HANDLING

How Supplied
Doxepin Hydrochloride Capsules, USP are available containing doxepin hydrochloride, USP equivalent to 10 mg, 25 mg, 50 mg, or 100 mg of doxepin.

The 10 mg capsules are hard-shell, gelatin capsules with a buff opaque cap and buff opaque body axially printed with MYLANover 1049in black ink on both the cap and the body. They are available as follows:

NDC 48433-035-20 – Unit dose blister packages of 100 (10 cards of 10 capsules each).

The 25 mg capsules are hard-shell, gelatin capsules with an ivory opaque cap and white opaque body axially printed with MYLANover 3125in black ink on both the cap and the body. They are available as follows:

NDC 48433-036-20 – Unit dose blister packages of 100 (10 cards of 10 capsules each).

The 50 mg capsules are hard-shell, gelatin capsules with an ivory opaque cap and ivory opaque body axially printed with MYLANover 4250in black ink on both the cap and the body. They are available as follows:

NDC 48433-037-20 – Unit dose blister packages of 100 (10 cards of 10 capsules each).

The 100 mg capsules are hard-shell, gelatin capsules with a brite lite green opaque cap and white opaque body axially printed with MYLANover 6410in black ink on both the cap and the body. They are available as follows:

NDC 48433-038-20 – Unit dose blister packages of 100 (10 cards of 10 capsules each).

Store at 20° to 25°C (68° to 77°F). [See USP Controlled Room Temperature.]
Protect from light.

PHARMACIST:Dispense a Medication Guide with each prescription.

17 PATIENT COUNSELING INFORMATION

Advise patients to read FDA-approved patient labeling (Medication Guide).

Suicidal Thoughts and Behaviors
Advise patients and caregivers to look for the emergence of suicidal thoughts and behaviors, especially early during doxepin hydrochloride capsules treatment and when the dosage is increased or decreased, and instruct them to report suicidal thinking and behavior to their health care provider [see Warnings and Precautions (5.1)].

Serotonin Syndrome
Caution patients about the risk of serotonin syndrome particularly with the concomitant use of doxepin hydrochloride capsules and other serotonergic drugs (e.g., other TCAs, SSRIs, SNRIs, triptans, opioids), lithium, tryptophan, buspirone, and St. John’s Wort and with drugs that impair metabolism of serotonin (in particular, MAOIs, both those intended to treat psychiatric disorders and also others, such as linezolid) [see Warnings and Precautions (5.2), Drug Interactions (7)]. Instruct patients to contact their health care provider or report to the emergency room if they experience signs or symptoms of serotonin syndrome.

Angle-Closure Glaucoma
Advise patients that taking doxepin hydrochloride capsules can cause pupillary dilation, which in susceptible individuals, can trigger angle closure glaucoma. Patients may wish to be examined to determine whether they are susceptible to angle closure, and have a prophylactic procedure (e.g., iridectomy), if they are susceptible [see Warnings and Precautions (5.3)] .

Effects on Driving and Operating Heavy Machinery
Inform patients that doxepin hydrochloride capsules can cause sedation and caution them against driving a car or operating dangerous machinery while taking doxepin hydrochloride capsules [see Warnings and Precautions (5.4)] .

Activation of Mania or Hypomania
Advise patients to observe for signs of mania/hypomania activation and instruct them to report such symptoms to the healthcare provider.

Drug Interactions
Inform patients that the use of doxepin hydrochloride capsules and certain other drugs increases the risk of doxepin hydrochloride capsule-associated adverse reactions or alternatively lower doxepin hydrochloride capsules effectiveness. Instruct patients to inform their healthcare provider about all the drugs that they are taking before taking doxepin hydrochloride capsules.

Alcohol Use
Advise patients to avoid the use of alcohol while taking doxepin hydrochloride capsules [see Drug Interactions (7)].

Pregnancy
Advise patients that there is a pregnancy exposure registry that monitors pregnancy outcomes in women exposed to doxepin hydrochloride capsules during pregnancy. Advise women to notify their healthcare provider if they become pregnant or intend to become pregnant during doxepin hydrochloride capsules treatment.

Advise pregnant women that doxepin hydrochloride capsules use late in pregnancy may increase the risk for neonatal complications requiring prolonged hospitalization, respiratory support, or tube feeding [see Use in Specific Populations (8.1)].

Lactation
Advise patients that breastfeeding is not recommended during doxepin hydrochloride capsules treatment [see Use in Specific Populations (8.2)] .

Medication Guide

Doxepin Hydrochloride Capsules, USP

(dox' e pin hye" droe klor' ide)

for oral use

What is the most important information I should know about doxepin hydrochloride capsules?

Doxepin hydrochloride capsules can cause serious side effects, including:

Increased risk of suicidal thoughts and actions.Doxepin hydrochloride capsules and other antidepressant medicines may increase the risk of suicidal thoughts and actions in people 24 years of age and younger, especially within the first few months of treatment or when the dose is changed. Doxepin hydrochloride capsules are not for use in children.

How can I watch for and try to prevent suicidal thoughts and actions in myself or a family member?

- Pay close attention to any changes, especially sudden changes in mood, behavior, thoughts, or feelings, or if you develop suicidal thoughts or actions. This is very important when an antidepressant medicine is started or when the dose is changed.
- Call your health care provider right away to report new or sudden changes in mood, behavior, thoughts, or feelings or if you develop suicidal thoughts or actions.
- Keep all follow-up visits with your health care provider as scheduled. Call your health care provider between visits as needed, especially if you have concerns about symptoms.

Call your health care provider or get emergency help right away if you or a family member have any of the following symptoms, especially if they are new, worse, or worry you:

- suicide attempts
- acting aggressive, being angry, or violent
- new or worse depression
- panic attacks
- new or worse irritability
- an extreme increase in activity or talking (mania)

- thoughts about suicide or dying
- acting on dangerous impulses
- new or worse anxiety
- feeling very agitated or restless
- trouble sleeping
- other unusual changes in behavior or mood

See “What are the possible side effects of doxepin hydrochloride capsules?”for more information about side effects.

What are doxepin hydrochloride capsules?

Doxepin hydrochloride capsules are a prescription medicine used to treat adults with a certain type of depression called major depressive disorder (MDD).

It is not known if doxepin hydrochloride capsules are safe and effective for use in children.

Do not take doxepin hydrochloride capsules if you:

- are allergic to doxepin, or any of the ingredients in doxepin hydrochloride capsules. See the end of this Medication Guide for a complete list of ingredients in doxepin hydrochloride capsules
- have glaucoma
- have or have had trouble urinating
- are taking, or have stopped taking within the last 14 days, a medicine called a Monoamine Oxidase Inhibitor (MAOI), including the antibiotic linezolid or intravenous methylene blue
  - Ask your health care provider or pharmacist if you are not sure if you are taking an MAOI, including the antibiotic linezolid or intravenous methylene blue
  - Do not start taking an MAOI for at least 14 days after you stop treatment with doxepin hydrochloride capsules

Before taking doxepin hydrochloride capsules, tell your health care provider about all your medical conditions, including if you:

- have, or have a family history of bipolar disorder, mania, or hypomania
- have or had depression, suicidal thoughts or behavior
- have kidney or liver problems
- have or had seizures or convulsions
- are pregnant or plan to become pregnant. Taking doxepin hydrochloride capsules during your third trimester of pregnancy may harm your unborn baby. Tell your health care provider if you become pregnant or think you may be pregnant during treatment with doxepin hydrochloride capsules
  - Babies born to mothers who take certain medicines, including doxepin hydrochloride capsules, during the third trimester of pregnancy may have symptoms of sedation, such as breathing problems, sluggishness, low muscle tone, feeding problems, and withdrawal symptoms. Talk to your health care provider about the risks to your unborn or newborn baby if you take doxepin hydrochloride capsules during pregnancy
  - There is a pregnancy registry for women who are exposed to doxepin hydrochloride capsules during pregnancy. The purpose of this registry is to collect information about the health of women exposed to doxepin hydrochloride capsules and their babies. If you become pregnant during treatment with doxepin hydrochloride capsules, talk to your health care provider about registering with the National Pregnancy Registry for Antidepressants. You can register by calling 1-866-961-2388 or visiting online at https://womensmentalhealth.org/clinical-and-research-programs/pregnancyregistry/antidepressants/
- are breastfeeding or plan to breastfeed. Doxepin hydrochloride can pass into your breast milk and harm your baby. Do not breastfeed during treatment with doxepin hydrochloride capsules. Talk to your health care provider about the best way to feed your baby during treatment with doxepin hydrochloride capsules

Tell your healthcare provider about all the medicines you take,including prescription and over-the-counter medicines, vitamins, and herbal supplements.

Doxepin hydrochloride capsules and other medicines may affect each other causing possible serious side effects. Doxepin hydrochloride capsules may affect the way other medicines work and other medicines may affect the way doxepin hydrochloride capsules work.

Especially tell your health care provider if you take:

- medicines used to treat mood, anxiety, psychotic, or thought disorders, including selective serotonin reuptake inhibitors (SSRIs) and serotonin norepinephrine reuptake inhibitors (SNRIs)
- medicines to treat migraine headaches known as triptans
- other tricyclic antidepressants
- tetracyclic antidepressants
- opioids
- lithium
- tryptophan
- buspirone
- St. John’s Wort
- carbamazepine
- cimetidine
- tolazamide
- medicines that can cause drowsiness

Ask your health care provider if you are not sure if you are taking any of these medicines. Your health care provider can tell you if it is safe to take doxepin hydrochloride capsules with your other medicines.

Do not start or stop any other medicines during treatment with doxepin hydrochloride capsules without first talking to your healthcare provider.

Know the medicines you take. Keep a list of them to show to your healthcare providers when you start to take a new medicine.

How should I take doxepin hydrochloride capsules?

- Take doxepin hydrochloride capsules exactly as your health care provider tells you to take them. Do not change your dose or stop taking doxepin hydrochloride capsules without first talking to your healthcare provider.
- Your health care provider may need to change the dose of doxepin hydrochloride capsules until it is the right dose for you.
- If you miss a dose of doxepin hydrochloride capsules, take the missed dose as soon as you remember. If it is almost time for the next dose, do not take the missed dose and take your next dose at the regular time. Do not take two doses of doxepin hydrochloride capsules at the same time.
- If you take too many doxepin hydrochloride capsules, call your healthcare provider or Poison Help Line at 1-800-222-1222 or go to the nearest hospital emergency room right away.

What should I avoid while taking doxepin hydrochloride capsules?

- Do not drive a car or another motor vehicle, operate heavy machinery, or do dangerous activities while taking doxepin hydrochloride capsules. Doxepin hydrochloride capsules can cause sleepiness or may affect your ability to make decisions, think clearly, or react quickly.
- Do not drink alcohol during treatment with doxepin hydrochloride capsules. Drinking alcohol during treatment with doxepin hydrochloride capsules can increase your risk of having serious side effects.

What are the possible side effects of doxepin hydrochloride capsules?

Doxepin hydrochloride capsules can cause serious side effects, including:

- See “What is the most important information I should know about doxepin hydrochloride capsules?”
- Serotonin syndrome.Taking doxepin hydrochloride capsules can cause a potentially life-threatening problem called serotonin syndrome. The risk of developing serotonin syndrome is increased when doxepin hydrochloride capsules are taken with certain other medicines. See “ Do not take doxepin hydrochloride capsules if you:” Stop taking doxepin hydrochloride capsules and call your healthcare provider or go to the nearest hospital emergency room right awayif you have any of the following signs and symptoms of serotonin syndrome:

- agitation
- confusion
- fast heartbeat
- dizziness
- flushing
- shaking (tremors), stiff muscles, or muscle twitching
- seizures

- seeing or hearing things that are not real (hallucinations)
- coma
- changes in blood pressure
- sweating
- high body temperature (hyperthermia)
- loss of coordination
- nausea, vomiting, diarrhea

- Eye problems (angle-closure glaucoma).Doxepin hydrochloride capsules may cause a type of eye problem called angle-closure glaucoma in people with certain eye problems. You may want to undergo an eye examination to see if you are at risk and receive preventative treatment if you are. Call your healthcare provider if you have eye pain, changes in your vision, or swelling or redness in or around the eye.
- Manic episodes.Manic episodes may happen in people with bipolar disorder who take doxepin hydrochloride capsules. Symptoms may include:

- greatly increased energy
- racing thoughts
- unusually grand ideas
- talking more or faster than usual

- severe trouble sleeping
- reckless behavior
- excessive happiness or irritability

- Seizures (convulsions)

The most common side effects of doxepin hydrochloride capsules include:

- feeling overly sleepy
- dry mouth
- dizziness

- constipation
- tiredness

These are not all the possible side effects of doxepin hydrochloride capsules.

Call your health care provider for medical advice about side effects. You may report side effects to FDA at 1-800-FDA1088.

How should I store doxepin hydrochloride capsules?

- Store doxepin hydrochloride capsules at controlled room temperature between 20° to 25°C (68° to 77°F).
- Keep doxepin hydrochloride capsules and all medicines out of the reach of children.

General Information about the safe and effective use of doxepin hydrochloride capsules.

Medicines are sometimes prescribed for purposes other than those listed in a Medication Guide. Do not take doxepin hydrochloride capsules for a condition for which they were not prescribed. Do not give doxepin hydrochloride capsules to other people, even if they have the same symptoms that you have. They may harm them. You can ask your pharmacist or healthcare provider for information about doxepin hydrochloride capsules that is written for health professionals.

What are the ingredients in doxepin hydrochloride capsules?

Active Ingredient:doxepin hydrochloride

Inactive Ingredients for Doxepin Hydrochloride Capsules:colloidal silicon dioxide, magnesium stearate, microcrystalline cellulose, pregelatinized starch (corn) and sodium lauryl sulfate. The empty gelatin capsule shells contain D&C Yellow No. 10, gelatin, sodium lauryl sulfate and titanium dioxide. In addition, the 10 mg, 25 mg and 50 mg empty gelatin capsule shells contain FD&C Yellow No. 6 and the 75 mg and 100 mg empty gelatin capsule shells contain FD&C Green No. 3.

The imprinting ink contains black iron oxide, D&C Yellow No. 10 Aluminum Lake, FD&C Blue No. 1 Aluminum Lake, FD&C Blue No. 2 Aluminum Lake, FD&C Red No. 40 Aluminum Lake, propylene glycol and shellac glaze.

For more information, contact Mylan at 1-877-446-3679 (1-877-4-INFO-RX).

This Medication Guide has been approved by the U.S. Food and Drug Administration .

Manufactured for:
Mylan Pharmaceuticals Inc.
Morgantown, WV 26505 U.S.A.

Distributed by:
Safecor Health LLC
Rockford, IL 61103 U.S.A.

Revised: 10/2025
VPL:DXPN:RX

PRINCIPAL DISPLAY PANEL – 10 mg

NDC 48433-035-20

Doxepin HCl
Capsules, USP
10 mg*

100 Capsules (10 x 10)

*Each capsule contains doxepin hydrochloride, USP
equivalent to 10 mg of doxepin.

Usual Daily Dosage:Mild to moderate symptomatology:
75 mg to 150 mg. Severe symptomatology: 150 mg to
300 mg. See package insert and Medication Guide for
complete dosage information.

Store at 20° to 25°C (68° to 77°F).
[See USP Controlled Room Temperature.]
Protect from light.

Manufactured for:
Mylan Pharmaceuticals Inc.
Morgantown, WV 26505 U.S.A.

Rx only

S-13411

Distributed by:

Safecor Health LLC

Rockford, IL 61103 U.S.A.

This unit dose package is not child resistant.

For institutional use only.

Keep this and all drugs out of the reach of children.

This container provides light-resistance.

See window for lot number and expiration date.

PRINCIPAL DISPLAY PANEL – 25 mg

NDC 48433-036-20

Doxepin HCl
Capsules, USP
25 mg*

100 Capsules (10 x 10)

*Each capsule contains doxepin hydrochloride, USP
equivalent to 25 mg of doxepin.

Usual Daily Dosage:Mild to moderate symptomatology:
75 mg to 150 mg. Severe symptomatology: 150 mg to
300 mg. See package insert and Medication Guide for
complete dosage information.

Store at 20° to 25°C (68° to 77°F).
[See USP Controlled Room Temperature.]
Protect from light.

Manufactured for:
Mylan Pharmaceuticals Inc.
Morgantown, WV 26505 U.S.A.

Rx only

S-13416

Distributed by:

Safecor Health LLC

Rockford, IL 61103 U.S.A.

This unit dose package is not child resistant.

For institutional use only.

Keep this and all drugs out of the reach of children.

This container provides light-resistance.

See window for lot number and expiration date.

PRINCIPAL DISPLAY PANEL – 50 mg

NDC 48433-037-20

Doxepin HCl
Capsules, USP
50 mg*

100 Capsules (10 x 10)
*Each capsule contains doxepin hydrochloride, USP
equivalent to 50 mg of doxepin.

Usual Daily Dosage:Mild to moderate symptomatology:
75 mg to 150 mg. Severe symptomatology: 150 mg to
300 mg. See package insert and Medication Guide for
complete dosage information.

Store at 20° to 25°C (68° to 77°F).
[See USP Controlled Room Temperature.]
Protect from light.

Manufactured for:
Mylan Pharmaceuticals Inc.
Morgantown, WV 26505 U.S.A.

Rx only

S-13421

Distributed by:

Safecor Health LLC

Rockford, IL 61103 U.S.A.

This unit dose package is not child resistant.

For institutional use only.

Keep this and all drugs out of the reach of children.

This container provides light-resistance.

See window for lot number and expiration date.

PRINCIPAL DISPLAY PANEL – 100 mg

NDC 48433-038-20

Doxepin HCl
Capsules, USP
100 mg*

100 Capsules (10 x 10)

*Each capsule contains doxepin hydrochloride, USP
equivalent to 100 mg of doxepin.

Usual Daily Dosage:Mild to moderate symptomatology:
75 mg to 150 mg. Severe symptomatology: 150 mg to
300 mg. See package insert and Medication Guide for
complete dosage information.

Store at 20° to 25°C (68° to 77°F).
[See USP Controlled Room Temperature.]
Protect from light.

Manufactured for:
Mylan Pharmaceuticals Inc.
Morgantown, WV 26505 U.S.A.

Rx only

S-13426

Distributed by:

Safecor Health LLC

Rockford, IL 61103 U.S.A.

This unit dose package is not child resistant.

For institutional use only.

Keep this and all drugs out of the reach of children.

This container provides light-resistance.

See window for lot number and expiration date.